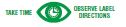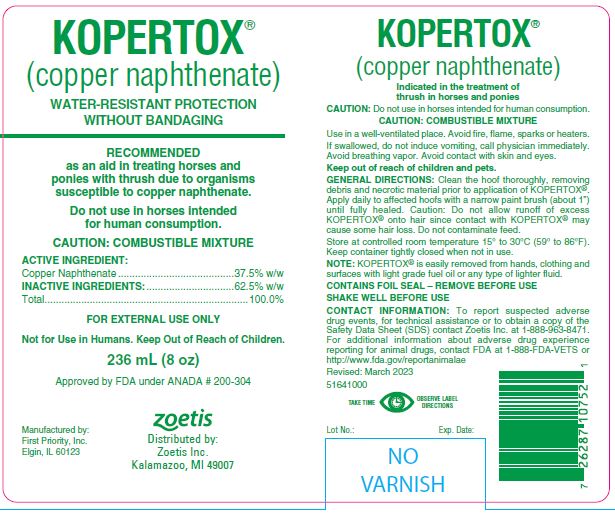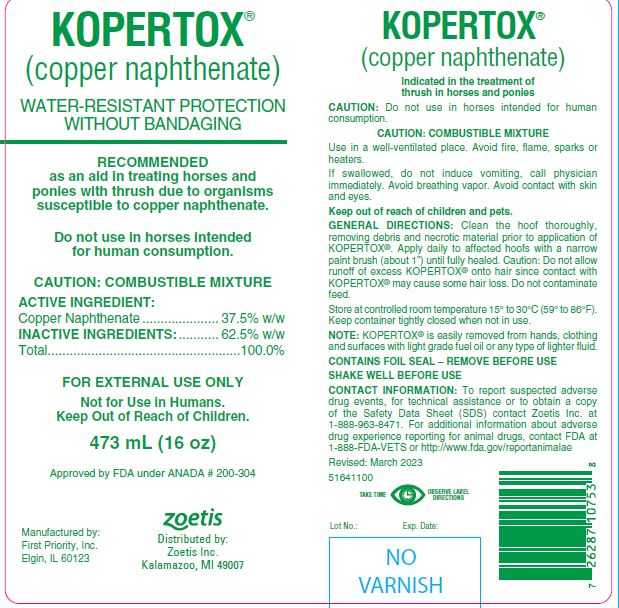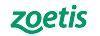 DRUG LABEL: KOPERTOX
NDC: 54771-1100 | Form: LIQUID
Manufacturer: Zoetis
Category: animal | Type: OTC ANIMAL DRUG LABEL
Date: 20231204

ACTIVE INGREDIENTS: COPPER NAPHTHENATE 0.825 g/1 mL

KOPERTOX®

INDICATIONS AND USAGE

(copper naphthenate)

WATER-RESISTANT PROTECTION WITHOUT BANDAGING

RECOMMENDED as an aid in treating horses and ponies with thrush due to organisms susceptible to copper naphthenate.

Do not use in horses intented for human consumption.

CAUTION: COMBUSTIBLE MIXTURE

ACTIVE INGREDIENT:

Copper Naphthenate ..................... 37.5% w/w

INACTIVE INGREDIENTS:

........... 62.5% w/w
Total .....................................................100.0%

PRECAUTIONS

FOR EXTERNAL USE ONLY
Not for Use in Humans.
Keep Out of Reach of Children.

INDICATIONS AND USAGE

Indicated in the treatment of thrush in horses and ponies

GENERAL PRECAUTIONS

CAUTION: Do not use in horses intended for human consumption.

CAUTION: COMBUSTIBLE MIXTURE

Use in a well-ventilated place. Avoid fire, flame, sparks or heaters.

If swallowed, do not induce vomiting, call physician immediately. Avoid breathing vapor. Avoid contact with skin and eyes.

Keep out of reach of children and pets.

GENERAL DIRECTIONS:

Clean the hoof thoroughly, removing debris and necrotic material prior to application of KOPERTOX®. Apply daily to affected hoofs with a narrow paint brush (about 1") until fully healed. Caution: Do not allow runoff of excess KOPERTOX® onto hair since contact with KOPERTOX® may cause some hair loss. Do not contaminate feed.

STORAGE AND HANDLING

Store at controlled room temperature 15° to 30°C (59° to 86°F). Keep container tightly closed when not in use.

INFORMATION FOR OWNERS/CAREGIVERS

NOTE: KOPERTOX® is easily removed from hands, clothing and surfaces with light grade fuel oil or any type of lighter fluid.

CONTAINS FOIL SEAL – REMOVE BEFORE USE.

SHAKE WELL BEFORE USE.

CONTACT INFORMATION:

To report suspected adverse drug events, for technical assistance or to obtain a copy of the Safety Data Sheet (SDS) contact Zoetis Inc. at
1-888-963-8471. For additional information about adverse drug experience reporting for animal drugs, contact FDA at 1-888-FDA-VETS or http://www.fda.gov/reportanimalae

HOW SUPPLIED

236 mL (8 oz) Rev. 03/2023 5164100

473 mL (16 oz) Rev. 03/2023 5161100

Approved by FDA under ANADA # 200-304

Distributed by:
Zoetis Inc.
Kalamazoo, MI 49007

Manufactured by:
First Priority, Inc.
Elgin, IL 60123